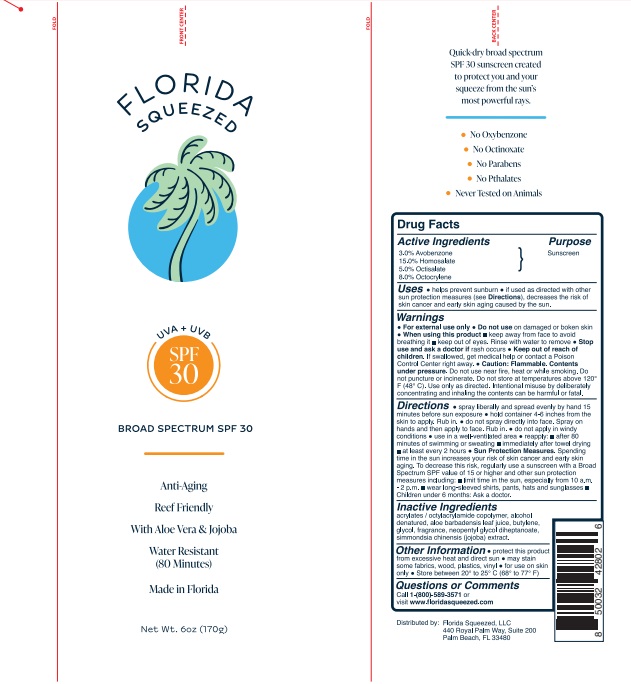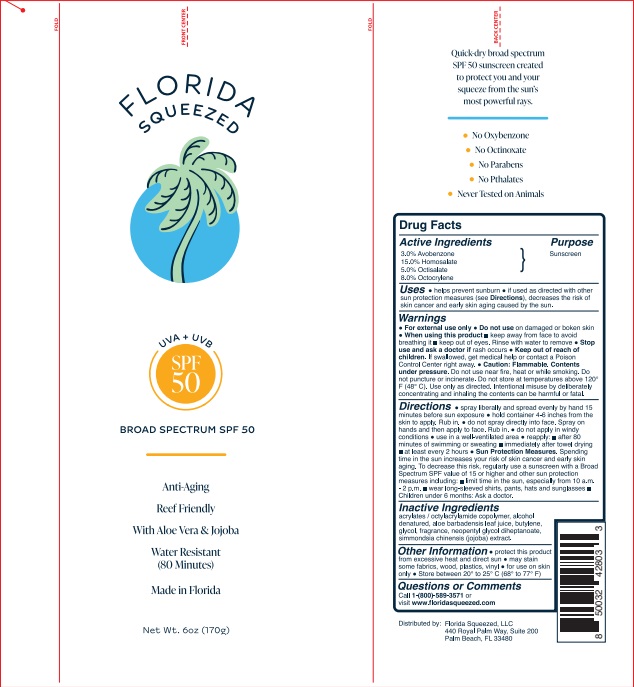 DRUG LABEL: Florida Squeeze SPF 50
NDC: 73440-2803 | Form: SPRAY
Manufacturer: Cross Brands Contract Filling
Category: otc | Type: HUMAN OTC DRUG LABEL
Date: 20210728

ACTIVE INGREDIENTS: HOMOSALATE 25.5 g/170 g; OCTOCRYLENE 13.6 g/170 g; AVOBENZONE 5.1 g/170 g; OCTISALATE 8.5 g/170 g
INACTIVE INGREDIENTS: ALCOHOL 104.55 g/170 g

Florida Squeeze Spray SPF 50 and SPF 30